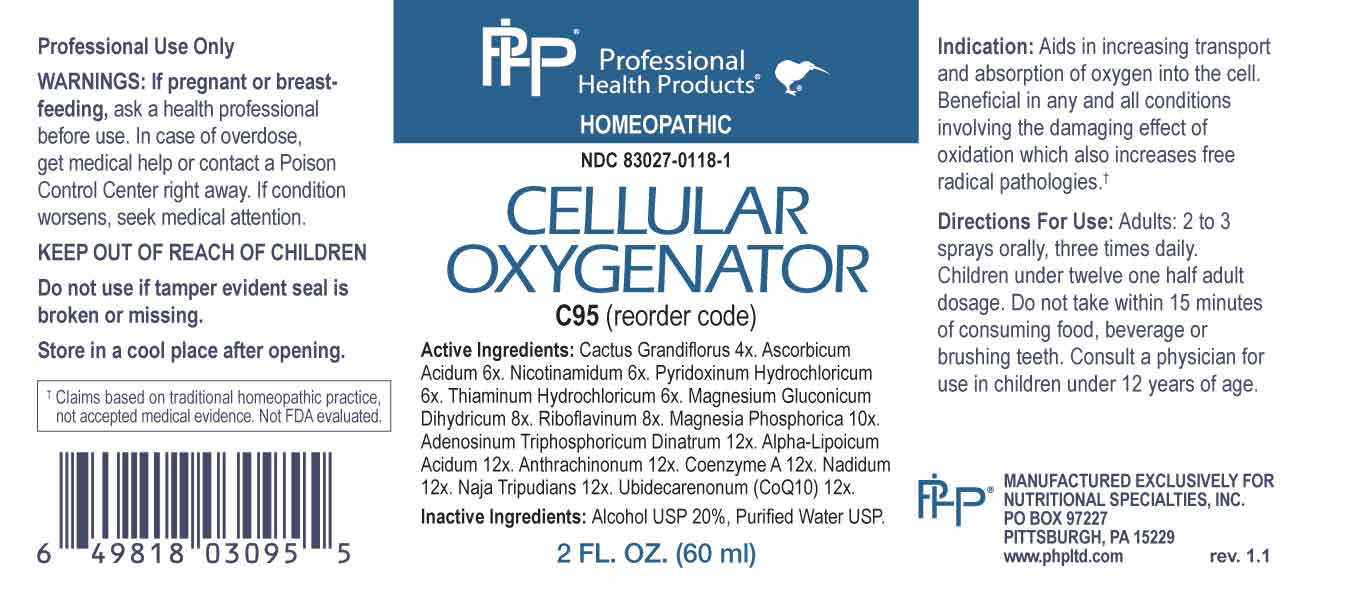 DRUG LABEL: Cellular Oxygenator
NDC: 83027-0118 | Form: SPRAY
Manufacturer: Nutritional Specialties, Inc.
Category: homeopathic | Type: HUMAN OTC DRUG LABEL
Date: 20231121

ACTIVE INGREDIENTS: SELENICEREUS GRANDIFLORUS STEM 4 [hp_X]/1 mL; ASCORBIC ACID 6 [hp_X]/1 mL; NIACINAMIDE 6 [hp_X]/1 mL; PYRIDOXINE HYDROCHLORIDE 6 [hp_X]/1 mL; THIAMINE HYDROCHLORIDE 6 [hp_X]/1 mL; MAGNESIUM GLUCONATE 8 [hp_X]/1 mL; RIBOFLAVIN 8 [hp_X]/1 mL; MAGNESIUM PHOSPHATE, DIBASIC TRIHYDRATE 10 [hp_X]/1 mL; ADENOSINE TRIPHOSPHATE DISODIUM 12 [hp_X]/1 mL; ALPHA LIPOIC ACID 12 [hp_X]/1 mL; ANTHRAQUINONE 12 [hp_X]/1 mL; COENZYME A 12 [hp_X]/1 mL; NADIDE 12 [hp_X]/1 mL; NAJA NAJA VENOM 12 [hp_X]/1 mL; UBIDECARENONE 12 [hp_X]/1 mL
INACTIVE INGREDIENTS: WATER; ALCOHOL

DRUG FACTS:

ACTIVE INGREDIENTS:

Cactus Grandiflorus 4X, Ascorbicum Acidum 6X, Nicotinamidum 6X, Pyridoxinum Hydrochloricum 6X, Thiaminum Hydrochloricum 6X, Magnesium Gluconicum Dihydricum 8X, Riboflavinum 8X, Magnesia Phosphorica 10X, Adenosinum Triphosphoricum Dinatrum 12X, Alpha-Lipoicum Acidum 12X, Anthrachinonum 12X, Coenzyme A 12X, Nadidum 12X, Naja Tripudians 12X, Ubidecarenonum (CoQ10) 12X.

PURPOSE:

Aids in increasing transport and absorption of oxygen into the cell. Beneficial in any and all conditions involving the damaging effect of oxidation which also increases free radical pathologies.†

†Claims based on traditional homeopathic practice, not accepted medical evidence. Not FDA evaluated.

WARNINGS:

Professional Use Only

If pregnant or breast-feeding, ask a health professional before use.

In case of overdose, get medical help or contact a Poison Control Center right away.

If condition worsens, seek medical attention.

KEEP OUT OF REACH OF CHILDREN

Do not use if tamper evident seal is broken or missing.

Store in a cool place after opening

KEEP OUT OF REACH OF CHILDREN:

In case of overdose, get medical help or contact a Poison Control Center right away.

DIRECTIONS:

Adults: 2 to 3 sprays orally, three times daily. Children under twelve one half adult dosage. Do not take within 15 minutes of consuming food, beverage or brushing teeth. Consult a physician for use in children under 12 years of age.

INDICATIONS:

Aids in increasing transport and absorption of oxygen into the cell. Beneficial in any and all conditions involving the damaging effect of oxidation which also increases free radical pathologies.†

†Claims based on traditional homeopathic practice, not accepted medical evidence. Not FDA evaluated.

INACTIVE INGREDIENTS:

Alcohol USP 20%, Purified Water USP.

QUESTIONS:

MANUFACTURED EXCLUSIVELY FOR

NUTRITIONAL SPECIALTIES, INC.

PO BOX 97227

PITTSBURG, PA 15229

www.phpltd.com

PACKAGE LABEL DISPLAY:

Professional

Health Products

HOMEOPATHIC

NDC 83027-0118-1

CELLULAR

OXYGENATOR

2 FL. OZ (60 ml)